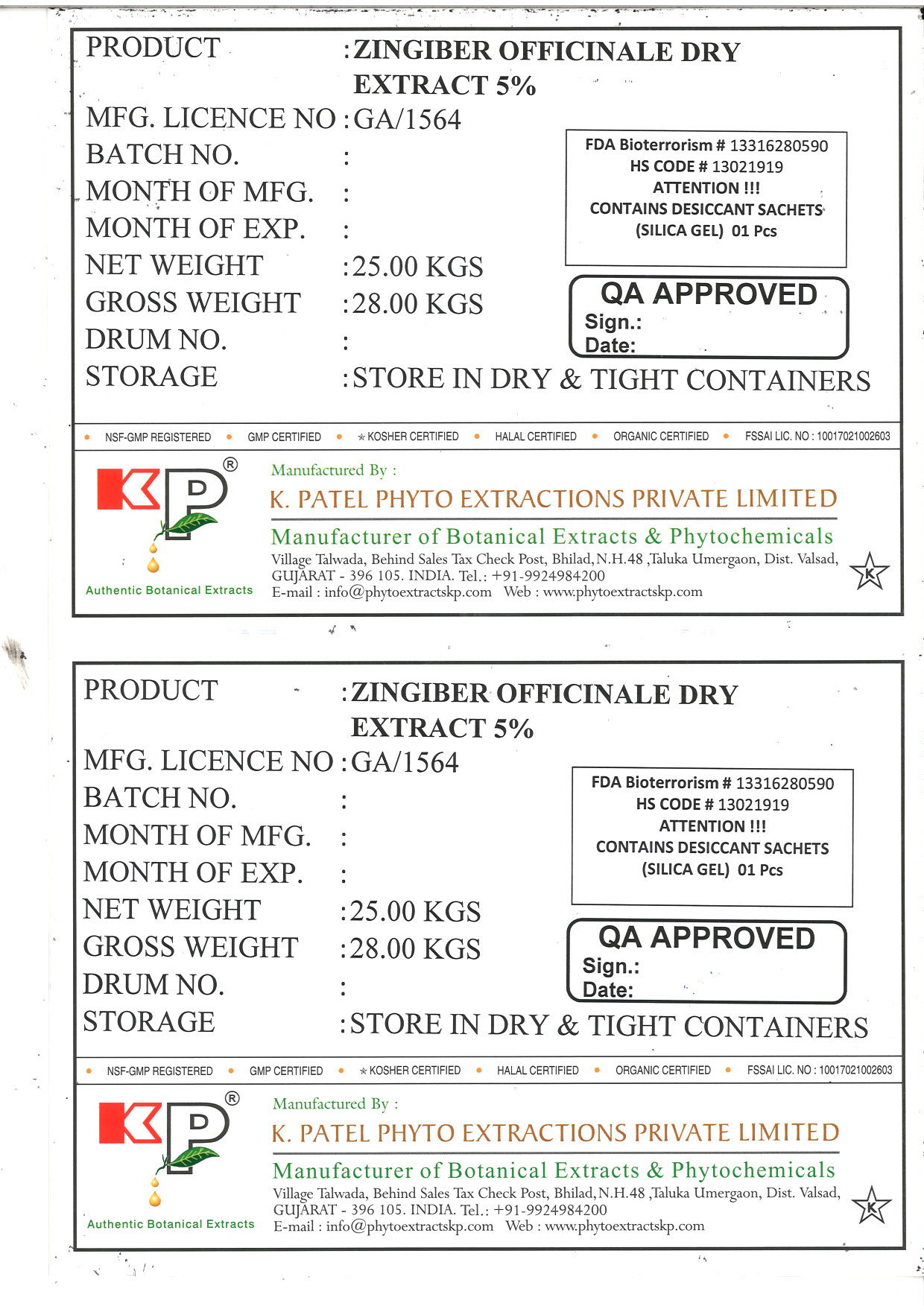 DRUG LABEL: Zingiber officinale dry extract 5%
NDC: 73276-006 | Form: POWDER
Manufacturer: K. Patel Phyto Extractions Private Limited
Category: other | Type: BULK INGREDIENT
Date: 20250625

ACTIVE INGREDIENTS: ZINGIBER OFFICINALE WHOLE 25 kg/25 kg

Zingiber officinale dry extract 5%